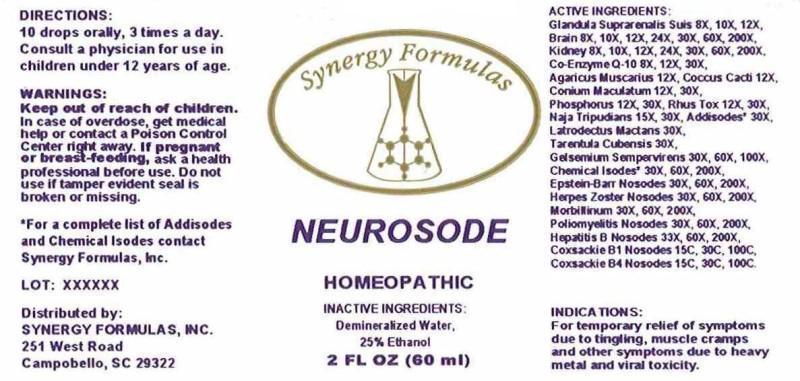 DRUG LABEL: Neurosode
NDC: 43772-0002 | Form: LIQUID
Manufacturer: Synergy Formulas, Inc
Category: homeopathic | Type: HUMAN OTC DRUG LABEL
Date: 20150120

ACTIVE INGREDIENTS: SUS SCROFA ADRENAL GLAND 8 [hp_X]/1 mL; PORK BRAIN 8 [hp_X]/1 mL; PORK KIDNEY 8 [hp_X]/1 mL; UBIDECARENONE 8 [hp_X]/1 mL; AMANITA MUSCARIA VAR. MUSCARIA FRUITING BODY 12 [hp_X]/1 mL; PROTORTONIA CACTI 12 [hp_X]/1 mL; CONIUM MACULATUM FLOWERING TOP 12 [hp_X]/1 mL; PHOSPHORUS 12 [hp_X]/1 mL; TOXICODENDRON PUBESCENS LEAF 12 [hp_X]/1 mL; NAJA NAJA VENOM 15 [hp_X]/1 mL; ASPARTAME 30 [hp_X]/1 mL; BENZALKONIUM CHLORIDE 30 [hp_X]/1 mL; FORMALDEHYDE 30 [hp_X]/1 mL; METHYLENE CHLORIDE 30 [hp_X]/1 mL; METHYLPARABEN 30 [hp_X]/1 mL; PROPYLPARABEN 30 [hp_X]/1 mL; SODIUM BENZOATE 30 [hp_X]/1 mL; SODIUM CITRATE 30 [hp_X]/1 mL; TITANIUM DIOXIDE 30 [hp_X]/1 mL; ZINC OXIDE 30 [hp_X]/1 mL; LATRODECTUS MACTANS 30 [hp_X]/1 mL; CITHARACANTHUS SPINICRUS 30 [hp_X]/1 mL; GELSEMIUM SEMPERVIRENS ROOT 30 [hp_X]/1 mL; SALICYLIC ACID 30 [hp_X]/1 mL; CORTICOTROPIN 30 [hp_X]/1 mL; CORTISONE ACETATE 30 [hp_X]/1 mL; EUGENOL 30 [hp_X]/1 mL; STEARYL ALCOHOL 30 [hp_X]/1 mL; XYLITOL 30 [hp_X]/1 mL; ESTRONE 30 [hp_X]/1 mL; BENZOIC ACID 30 [hp_X]/1 mL; CHLORINE 30 [hp_X]/1 mL; POTASSIUM SORBATE 30 [hp_X]/1 mL; SORBITOL 30 [hp_X]/1 mL; RESORCINOL 30 [hp_X]/1 mL; BENZYL ALCOHOL 30 [hp_X]/1 mL; LACTIC ACID, DL- 30 [hp_X]/1 mL; ISOPROPYL PALMITATE 30 [hp_X]/1 mL; BORIC ACID 30 [hp_X]/1 mL; ACETIC ACID 30 [hp_X]/1 mL; PHENYLBUTAZONE 30 [hp_X]/1 mL; PETROLATUM 30 [hp_X]/1 mL; LEAD 30 [hp_X]/1 mL; HUMAN HERPESVIRUS 4 30 [hp_X]/1 mL; HUMAN HERPESVIRUS 3 30 [hp_X]/1 mL; MEASLES VIRUS 30 [hp_X]/1 mL; POLIOVIRUS 30 [hp_X]/1 mL; HEPATITIS B VIRUS 30 [hp_X]/1 mL; HUMAN COXSACKIEVIRUS B1 15 [hp_C]/1 mL; HUMAN COXSACKIEVIRUS B4 15 [hp_C]/1 mL
INACTIVE INGREDIENTS: WATER; ALCOHOL

DRUG FACTS:

ACTIVE INGREDIENTS:

Glandula Suprarenalis Suis 8X, 10X, 12X, Brain (Suis) 8X, 10X, 12X, 24X, 30X, 60X, 200X, Kidney (Suis) 8X, 10X, 12X, 24X, 30X, 60X, 200X, Co-Enzyme Q-10 8X, 12X, 30X, Agaricus Muscarius 12X, Coccus Cacti 12X, Conium Maculatum 12X, 30X, Phosphorus 12X, 30X, Rhus Tox 12X, 30X, Naja Tripudians 15X, 30X, Aspartame 30X, Benzalkonium Chloride 30X, Formalinum 30X, Methylene Chloride 30X, Methyl Paraben 30X, Propyl Paraben 30X, Sodium Benzoate 30X, Sodium Citrate 30X, Titanium Dioxide 30X, Zicum Oxydatum 30X, Latrodectus Mactans 30X, Tarentula Cubensis 30X, Gelsemium Sempervirens 30X, 60X, 100X, Salicylicum Acidum 30X, 60X, 200X, Adrenocorticotrophin 30X, 60X, 200X, Cortisone Aceticum 30X, 60X, 200X, Eugenol 30X, 60X, 200X, Stearyl Alcohol 30X, 60X, 200X, Xylitol 30X, 60X, 200X, Folliculinum 30X, 60X, 200X, Benzoicum Acidum 30X, 60X, 200X, Chlorinum 30, 60X, 200X, Potassium Sorbate 30X, 60X, 200X, Sorbitol 30X, 60X, 200X, Resorcinum 30X, 60X, 200X, Benzyl Alcohol 30X, 60X, 200X, Lacticum Acidum 30X, 60X, 200X, Isopropyl Palmitate 30X, 60X, 200X, Boricum Acidum 30X, 60X, 200X, Aceticum Acidum 30X, 60X, 200X, Phenyl Butazone 30X, 60X, 200X, Petroleum Jelly 30X, 60X, 200X, Plumbum Metallicum 30X, 60X, 200X, Epstein-Barr Virus 30X, 60X, 200X, Herpes Zoster 30X, 60X, 200X, Morbillinum 30X, 60X, 200X, Poliomyelitis Nosodes 30X, 60X, 200X, Hepatitis B Nosodes 33X, 60X, 200X, Coxsackie B1 Nosodes 15C, 30C, 100C, Coxsackie B4 Nosodes 15C, 30C, 100C

INDICATIONS:

For temporary relief of symptoms due to tingling, muscle cramps and other symptoms due to heavy metal, and viral toxicity.

WARNINGS:

Keep out of reach of children. In case of overdose, get medical help or contact a Poison Control Center right away.

If pregnant or breast-feeding, ask a health care professional before use.

Do not use if tamper evident seal is broken or missing.

Keep out of reach of children. In case of overdose, get medical help of consult a Poison Control Center right away.

DIRECTIONS:

10 drops orally, 3 times a day. Consult a physician for use in children under 12 years of age.

INDICATIONS:

For temporary relief of symptoms due to tingling, muscle cramps and other symptoms due to heavy metal, and viral toxicity.

INACTIVE INGREDIENTS:

Demineralized Water, 25% Ethanol.

QUESTIONS:

Distributed by:

SYNERGY FORMULAS, INC.

251 West Road

Campobello, SC 29322

*For a complete list of Addisodes and Chemical Isodes contact Synergy Formulas, Inc.

PACKAGE LABEL DISPLAY:

Synergy Formulas

NEUROSODE

2 FL OZ (60 ml)